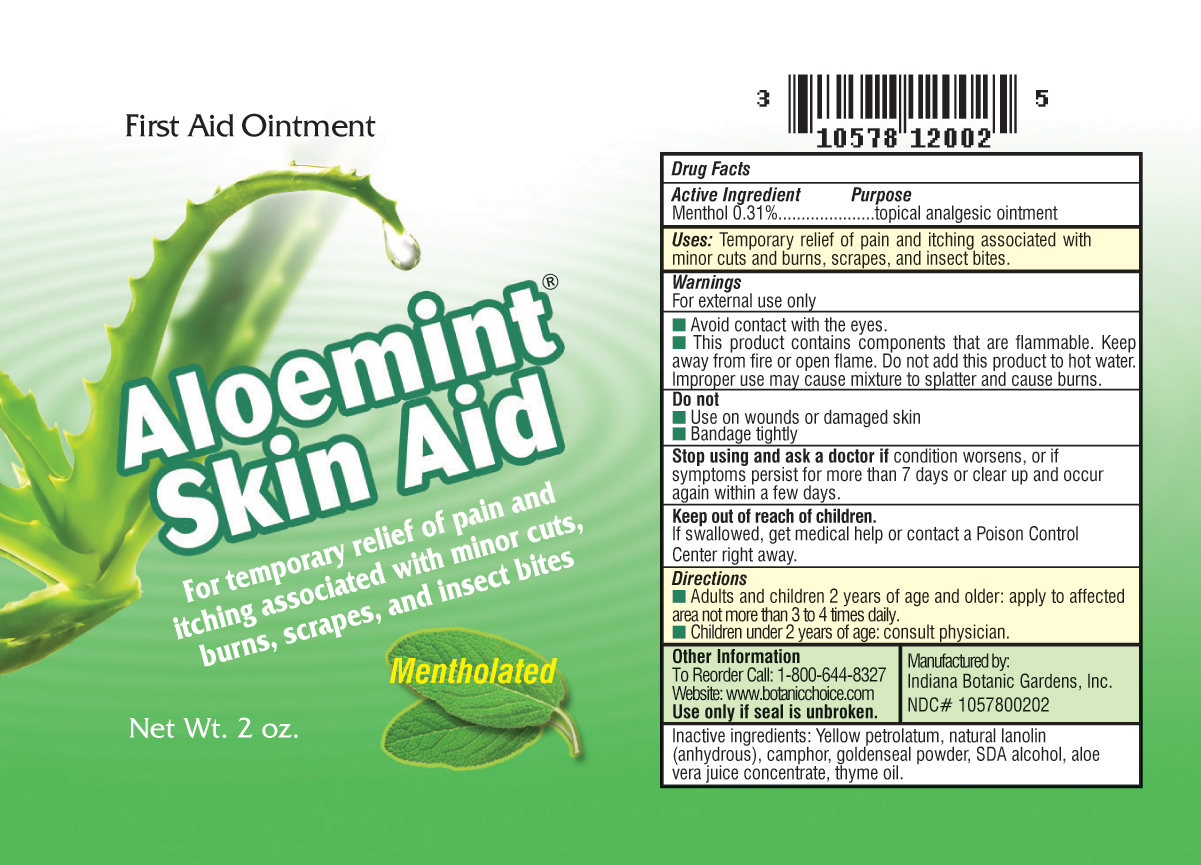 DRUG LABEL: Aloemint Skin Aid
NDC: 10578-002 | Form: OINTMENT
Manufacturer: Indiana Botanic Gardens
Category: otc | Type: HUMAN OTC DRUG LABEL
Date: 20100721

ACTIVE INGREDIENTS: MENTHOL 0.31 g/100 g
INACTIVE INGREDIENTS: PETROLATUM; LANOLIN; CAMPHOR (SYNTHETIC); GOLDENSEAL; ALCOHOL; ALOE VERA LEAF; THYME OIL

Aloemint Skin Aid

Active Ingredient Purpose

Menthol 0.31% topical analgesic ointment

INDICATIONS AND USAGE

Uses: Temporary relief of pain and itching associated with minor cuts and burns, scrapes, and insect bites.

Warnings: For external use only.

Avoid contact with the eyes.

This product contains components that are flammable. Keep away from fire or open flame. Do not add this product to hot water. Improper use may cause mixture to splatter and cause burns.

Do not:

use on wounds or damaged skin

bandage tightly

ASK DOCTOR

Stop using and ask a doctor if condition worsens, or if symptoms persist for more than 7 days or clear up and occur again within a few days.

Keep out of reach of children. If swallowed, get medical help or contact a Poison Control Center right away.

Directions:

Adults and children 2 years of age and older: apply to affected area not more than 3 to 4 times daily.

Children under 2 years of age: consult physician.

Other information:

To reorder call: 1-800-644-8327

website: www.botanicchoice.com

Use only of seal is unbroken

Manufactured by: Indiana Botanic Gardens, Inc.

NDC# 1057800202

INACTIVE INGREDIENT

Inactive ingredients: yellow petrolatum, natural lanolin (anhydrous), camphor, goldenseal powder, SDA alcohol, aloe vera juice concentrate, thyme oil